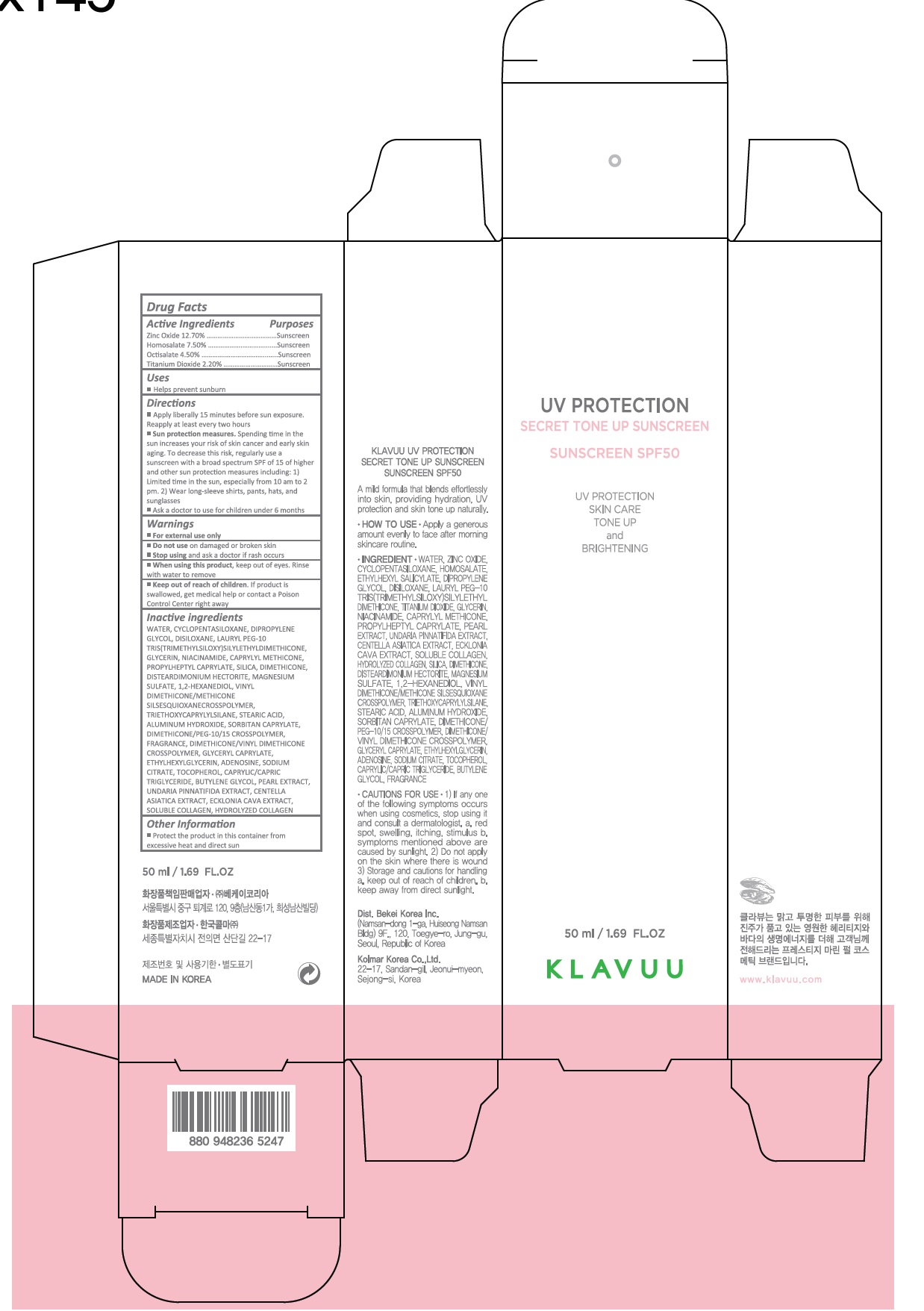 DRUG LABEL: KLAVUU UV Protection Secret Tone Up Sunscreen
NDC: 70976-007 | Form: CREAM
Manufacturer: Bekeikorea
Category: otc | Type: HUMAN OTC DRUG LABEL
Date: 20210412

ACTIVE INGREDIENTS: ZINC OXIDE 6.35 mg/50 mL; HOMOSALATE 3.75 mg/50 mL; OCTISALATE 2.25 mg/50 mL; TITANIUM DIOXIDE 1.1 mg/50 mL
INACTIVE INGREDIENTS: WATER; CYCLOMETHICONE 5; DIPROPYLENE GLYCOL; HEXAMETHYLDISILOXANE; GLYCERIN; NIACINAMIDE; CAPRYLYL TRISILOXANE; PROPYLHEPTYL CAPRYLATE; SILICON DIOXIDE; DIMETHICONE; DISTEARDIMONIUM HECTORITE; MAGNESIUM SULFATE, UNSPECIFIED FORM; 1,2-HEXANEDIOL; TRIETHOXYCAPRYLYLSILANE; STEARIC ACID; ALUMINUM HYDROXIDE; SORBITAN MONOCAPRYLATE; DIMETHICONE/PEG-10/15 CROSSPOLYMER; DIMETHICONE/VINYL DIMETHICONE CROSSPOLYMER (HARD PARTICLE); GLYCERYL MONOCAPRYLATE; ETHYLHEXYLGLYCERIN; ADENOSINE; SODIUM CITRATE, UNSPECIFIED FORM; TOCOPHEROL; MEDIUM-CHAIN TRIGLYCERIDES; BUTYLENE GLYCOL; UNDARIA PINNATIFIDA; CENTELLA ASIATICA WHOLE; ECKLONIA CAVA

70976-007_KLAVUU UV Protection Secret Tone Up Sunscreen

ACTIVE INGREDIENT

Zinc Oxide 12.70%

Homosalate 7.50%

Octisalate 4.50%

Titanium Dioxide 2.20%

PURPOSE

Sunscreen

INDICATIONS AND USAGE

Helps prevent sunburn

DOSAGE AND ADMINISTRATION

Apply liberally 15 minutes before sun exposure. Reapply at least every two hours

Sun protection measures. Spending time in the sun increases your risk of skin cancer and early skin aging. To decrease this risk, regularly use a sunscreen with a broad spectrum SPF of 15 of higher and other sun protection measures including: 1) Limited time in the sun, especially from 10 am to 2 pm. 2) Wear long-sleeve shirts, pants, hats, and sunglasses

Ask a doctor to use for children under 6 months

WARNINGS

For external use only

Do not use on damaged or broken skin

When using this product, keep out of eyes. Rinse with water to remove.

Stop using and ask a doctor if rash occurs.

KEEP OUT OF REACH OF CHILDREN

Keep out of reach of the children. If product is swallowed, get medical help or contact a poison control center right away.

INACTIVE INGREDIENT

WATER, CYCLOPENTASILOXANE, DIPROPYLENE GLYCOL, DISILOXANE, LAURYL PEG-10 TRIS(TRIMETHYLSILOXY)SILYLETHYLDIMETHICONE, GLYCERIN, NIACINAMIDE, CAPRYLYL METHICONE, PROPYLHEPTYL CAPRYLATE, SILICA, DIMETHICONE, DISTEARDIMONIUM HECTORITE, MAGNESIUM SULFATE, 1,2-HEXANEDIOL, VINYL DIMETHICONE/METHICONE SILSESQUIOXANECROSSPOLYMER, TRIETHOXYCAPRYLYLSILANE, STEARIC ACID, ALUMINUM HYDROXIDE, SORBITAN CAPRYLATE, DIMETHICONE/PEG-10/15 CROSSPOLYMER, FRAGRANCE, DIMETHICONE/VINYL DIMETHICONE CROSSPOLYMER, GLYCERYL CAPRYLATE, ETHYLHEXYLGLYCERIN, ADENOSINE, SODIUM CITRATE, TOCOPHEROL, CAPRYLIC/CAPRIC TRIGLYCERIDE, BUTYLENE GLYCOL, PEARL EXTRACT, UNDARIA PINNATIFIDA EXTRACT, CENTELLA ASIATICA EXTRACT, ECKLONIA CAVA EXTRACT, SOLUBLE COLLAGEN, HYDROLYZED COLLAGEN